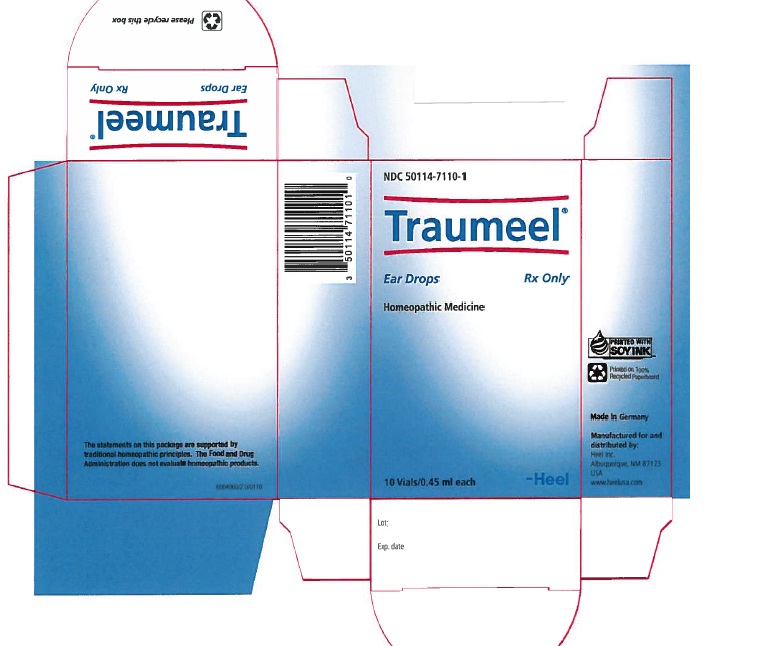 DRUG LABEL: Traumeel
NDC: 50114-7110 | Form: SOLUTION/ DROPS
Manufacturer: Heel Inc
Category: homeopathic | Type: HUMAN PRESCRIPTION DRUG LABEL
Date: 20120523

ACTIVE INGREDIENTS: ARNICA MONTANA ROOT 3 [hp_X]/0.45 mL; ATROPA BELLADONNA 3 [hp_X]/0.45 mL; ACONITUM NAPELLUS 3 [hp_X]/0.45 mL; HYPERICUM PERFORATUM 3 [hp_X]/0.45 mL; CALENDULA OFFICINALIS FLOWERING TOP 2 [hp_X]/0.45 mL; MATRICARIA RECUTITA 3 [hp_X]/0.45 mL; ACHILLEA MILLEFOLIUM 3 [hp_X]/0.45 mL; CALCIUM SULFIDE 6 [hp_X]/0.45 mL; COMFREY ROOT 6 [hp_X]/0.45 mL; BELLIS PERENNIS 2 [hp_X]/0.45 mL; MERCURIUS SOLUBILIS 6 [hp_X]/0.45 mL; ECHINACEA, UNSPECIFIED 2 [hp_X]/0.45 mL; ECHINACEA PURPUREA 2 [hp_X]/0.45 mL; HAMAMELIS VIRGINIANA ROOT BARK/STEM BARK 1 [hp_X]/0.45 mL
INACTIVE INGREDIENTS: SODIUM CHLORIDE

Traumeel Ear Drops Rx

DESCRIPTION

Traumeel Ear Drops Rx is a liquid homeopathic drug for otic administration. Each 0.45 ml vial contains Active Ingredients: Arnica montana, radix 3X 9.9 mcl, Belladonna 3X 9.9 mcl, Aconitum napellus 3X 9.54 mcl, Hypericum perforatum 3X 2.97 mcl, Calendula officinalis 2X 0.99 mcl, Chamomilla 3X 0.99 mcl, Millefolium 3X 0.99 mcl, Hepar sulphuris calcareum 6X 0.99 mcl, Symphytum officinale 6X 0.99 mcl, Bellis perennis 2X 0.495 mcl, Mercurius solubilis 6X 0.495 mcl, Echinacea 2X 0.247 mcl, Echinacea purpurea 2X 0.247 mcl, Hamamellis virginiana 1X 0.099 mcl Inactive Ingredients: Isotonic Sodium Chloride Solution.

INDICATIONS AND USAGE

Traumeel Ear Drops Rx is indicated for the treatment of pain due to inflammation of otitis media and externa.

DOSAGE AND ADMINISTRATION

Adults and children 6 years and over: pour contents of 1 vial directly into the affected ear up to 3 times daily. Infants and children under 6 years: pour 1/2 of the contents of 1 vial into the affected ear up to 3 times daily.

WARNINGS AND PRECAUTIONS

No harmful or potentially harmful side effects are known. Traumeel ear drops is generally well-tolerated, however if symptoms persist or worsen, discontinue use.
To report SUSPECTED ADVERSE REACTIONS, contact Heel Inc. at 1.800.920.9203 or info@heelusa.com or FDA at 1-800-FDA-1088 or www.fda.gov/medwatch